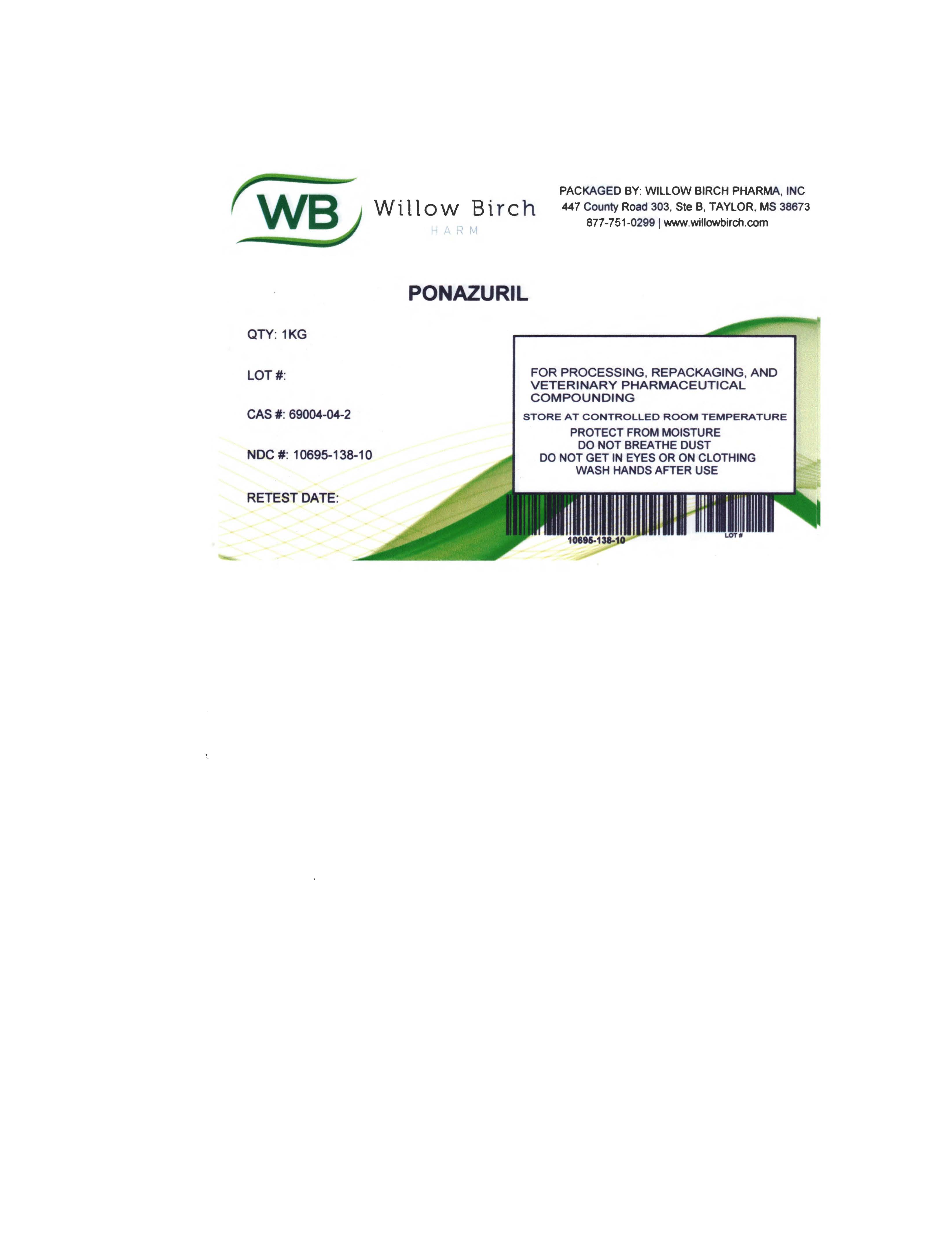 DRUG LABEL: Ponazuril
NDC: 10695-138 | Form: POWDER
Manufacturer: Willow Birch Pharma, Inc.
Category: other | Type: BULK INGREDIENT - ANIMAL DRUG
Date: 20220920

ACTIVE INGREDIENTS: PONAZURIL 1 kg/1 kg

Ponazuril